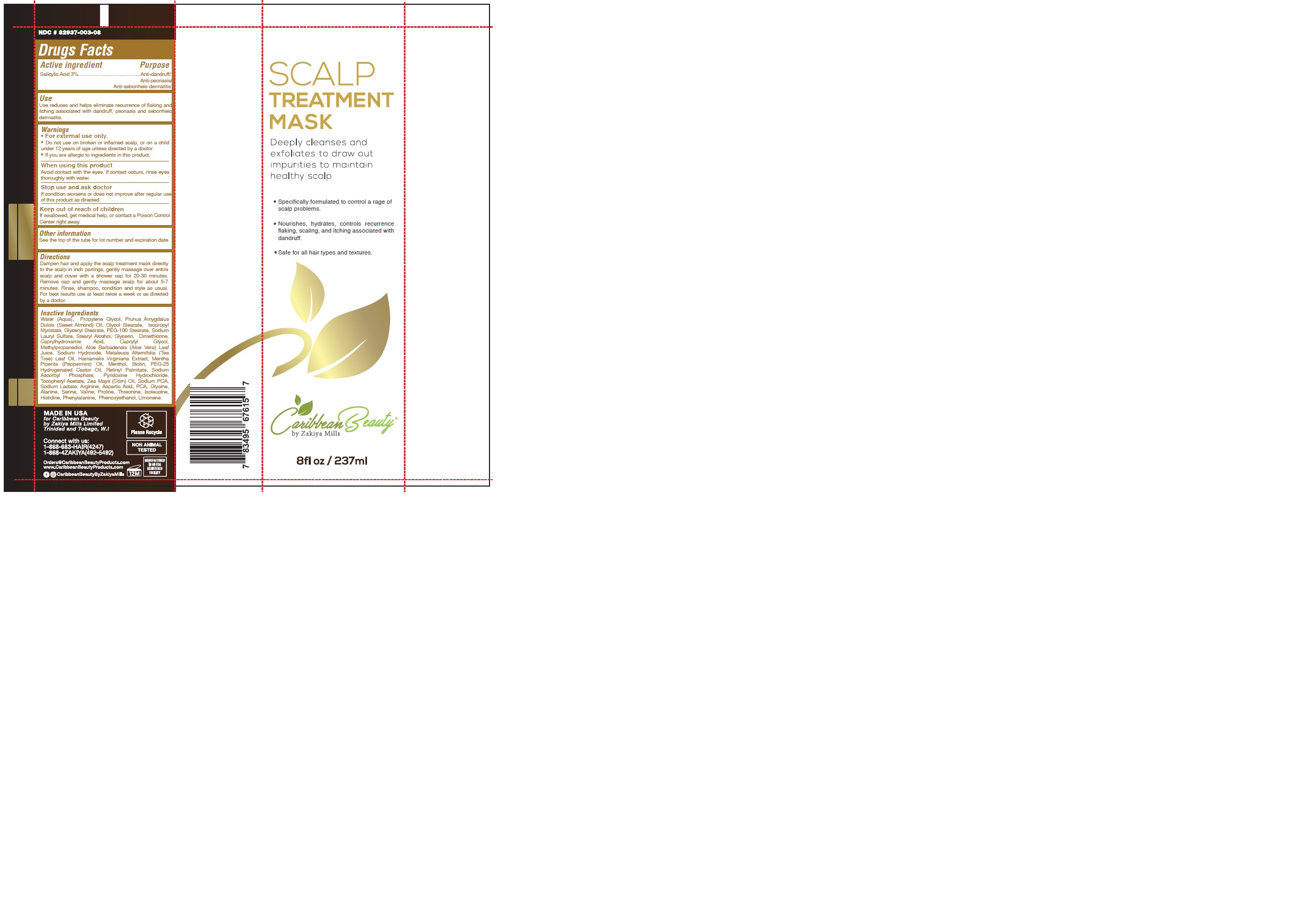 DRUG LABEL: CARIBBEAN BEAUTY - SCALP TREATMENT MASK
NDC: 82937-003 | Form: CREAM
Manufacturer: ZM Group of companies
Category: otc | Type: HUMAN OTC DRUG LABEL
Date: 20231004

ACTIVE INGREDIENTS: SALICYLIC ACID 7.0753 g/237 mL
INACTIVE INGREDIENTS: ALPHA-TOCOPHEROL ACETATE; SODIUM LACTATE; CAPRYLHYDROXAMIC ACID; PROPYLENE GLYCOL; GLYCERYL STEARATE/PEG-100 STEARATE; GLYCERIN; CAPRYLYL GLYCOL; GLYCINE; GLYCOL STEARATE; SODIUM LAURYL SULFATE; ALMOND OIL; THREONINE; PHENYLALANINE; HISTIDINE; SODIUM HYDROXIDE; SODIUM PYRROLIDONE CARBOXYLATE; WATER; DIMETHICONE 350; PHENOXYETHANOL; METHYLPROPANEDIOL; TEA TREE OIL; PYRROLIDONE CARBOXYLIC ACID; BIOTIN; PYRIDOXINE HYDROCHLORIDE; ARGININE; ISOLEUCINE; LIMONENE, (+)-; ISOPROPYL MYRISTATE; STEARYL ALCOHOL; ALOE VERA LEAF; VALINE; CORN OIL; ASPARTIC ACID; ALANINE; SERINE; PEG-25 HYDROGENATED CASTOR OIL; HAMAMELIS VIRGINIANA LEAF; PEPPERMINT OIL; MENTHOL; VITAMIN A PALMITATE; SODIUM ASCORBYL PHOSPHATE; PROLINE

82937-003-08

ACTIVE INGREDIENT

Salicylic Acid 3%

PURPOSE

Anti-dandruff

Anti-psoriasis

Anti-seborrheic dermatitis

INDICATIONS AND USAGE

Use reduces and helps eliminate recurrence of flaking and itching associated with dandruff, psoriasis and seborrheic dermatitis.

WARNINGS

For external use only.

Do not use on broken or inflamed scalp, or on a child under 12 years of age unless directed by a doctor

If you are allergic to ingredients in this product

WHEN USING

Avoid contact with the eyes. If contact occurs, rinse eyes thoroughly with water.

Stop use and ask doctor

If condition worsens or does not improve after regular use of this product as directed.

KEEP OUT OF REACH OF CHILDREN

If swallowed, get medical help, or contact a Poison Control Center right away.

DOSAGE AND ADMINISTRATION

Dampen hair and apply the scalp treatment mask directly to the scalp in inch partings, gently massage over entire scalp and cover with a shower cap for 20-30 minutes. Remove cap and gently massage scalp for about 5-7 minutes. Rinse, shampoo, condition and style as usual. For best results use at least twice a week or as directed by a doctor.

OTHER SAFETY INFORMATION

See the top of the tube for lot number and expiration date.

INACTIVE INGREDIENT

Water (Aqua), Propylene Glycol, Prunus Amygdalus Dulcis (Sweet Almond) Oil, Glycol Stearate, Isopropyl Myristate, Glyceryl Stearate, PEG-100 Stearate, Sodium Lauryl Sulfate, Stearyl Alcohol, Glycerin, Dimethicone, Caprylhydroxamic Acid, Caprylyl Glycol, Methylpropanediol, Aloe Barbadensis (Aloe Vera) Leaf Juice, Sodium Hydroxide, Melaleuca Alternifolia (Tea Tree) Leaf Oil, Hamamelis Virginiana Extract, Mentha Piperita (Peppermint) Oil, Menthol, Biotin, PEG-25 Hydrogenated Castor Oil, Retinyl Palmitate, Sodium Ascorbyl Phosphate, Pyridoxine Hydrochloride, Tocopheryl Acetate, Zea Mays (Corn) Oil, Sodium PCA, Sodium Lactate, Arginine, Aspartic Acid, PCA, Glycine, Alanine, Serine, Valine, Proline, Threonine, Isoleucine, Histidine, Phenylalanine, Phenoxyethanol, Limonene.